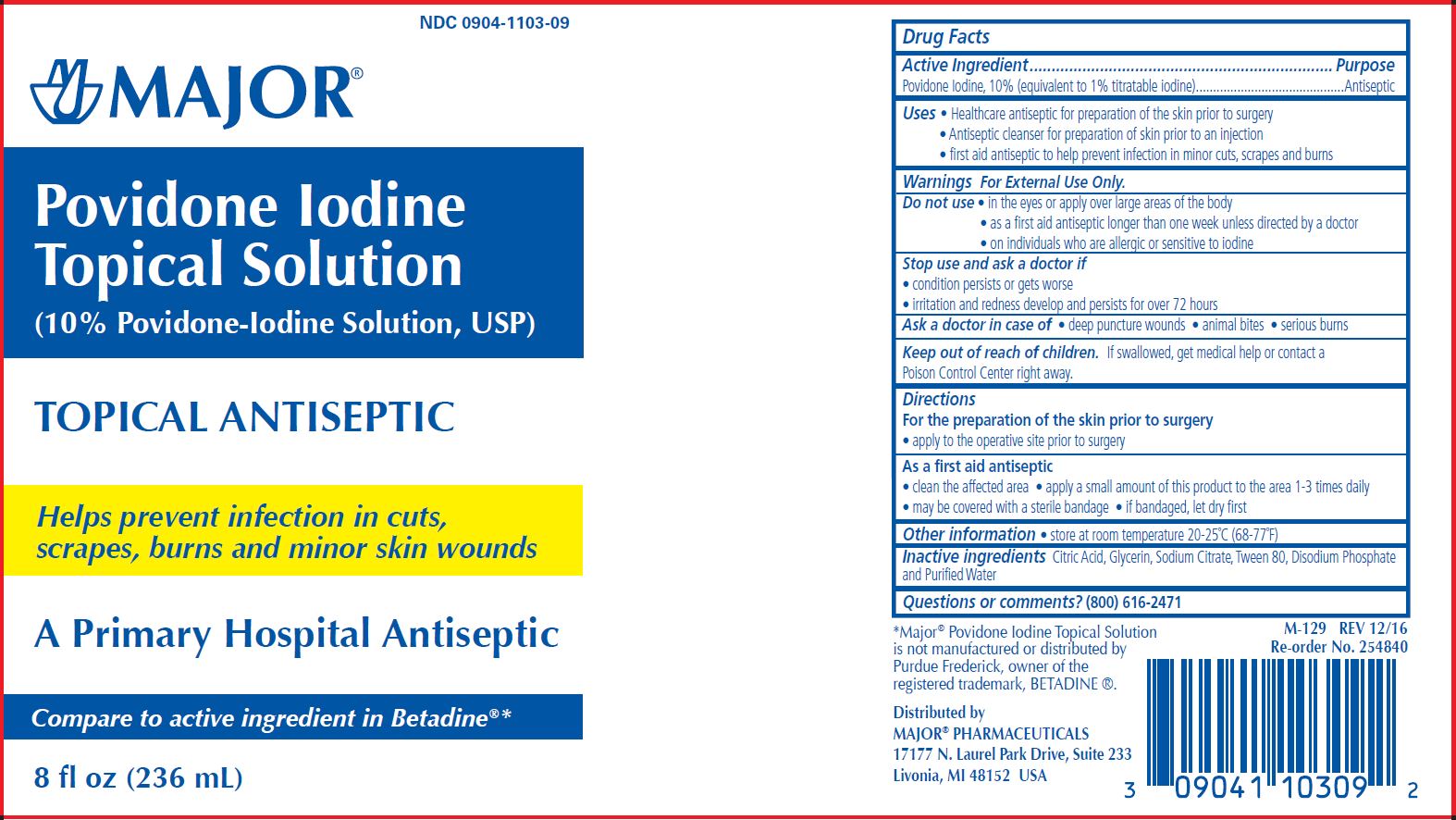 DRUG LABEL: povidone iodine
NDC: 0904-1103 | Form: SOLUTION
Manufacturer: Major Pharmaceuticals
Category: otc | Type: HUMAN OTC DRUG LABEL
Date: 20250402

ACTIVE INGREDIENTS: POVIDONE-IODINE 100 mg/1 mL
INACTIVE INGREDIENTS: CITRIC ACID MONOHYDRATE; WATER; GLYCERIN; SODIUM CITRATE; POLYSORBATE 80; SODIUM PHOSPHATE

Povidone Iodine Prep

Active ingredient

Active Ingredient Purpose

Povidone Iodine 10% v/v Antiseptic

Uses

- First aid antiseptic to help prevent infection in minor cuts, scrapes and burns.
- Healthcare antiseptic for preparation of the skin prior to surgery.
- Antiseptic cleanser for preparation of skin prior to an infection.

Warnings

- FOR EXTERNAL USE ONLY

Do not use

- As a first aid antiseptic for more than 1 week unless directed by a doctor.
- In the eyes.
- Over large areas of the body.
- On individuals who are allergic or sensitive to iodine.

Ask a doctor before use if you have

- Deep puncture wounds
- Animal bites
- Serious burns

Stop Use

- If irritation and redness develop
- If condition persists for more than 72 hours, consult a physician.

Keep out of reach of children.If swallowed, get medical help or contact a Poison Control Center.

Directions

As a first aid antiseptic

- clean affected area
- apply a small amount of this product to the area1 to 3 times daily
- may be covered with a sterile bandage, if bandaged let dry.

For preoperative patient skin preparation

- clean area
- apply to operative site prior to surgery using the applicator

Inactive Ingredient

- citric acid
- glycerin
- sodium citrate
- tween 80
- disodium phosphate
- purified Water

INDICATIONS AND USAGE

For use as an

- first aid antiseptic
- pre-operative skin preperation